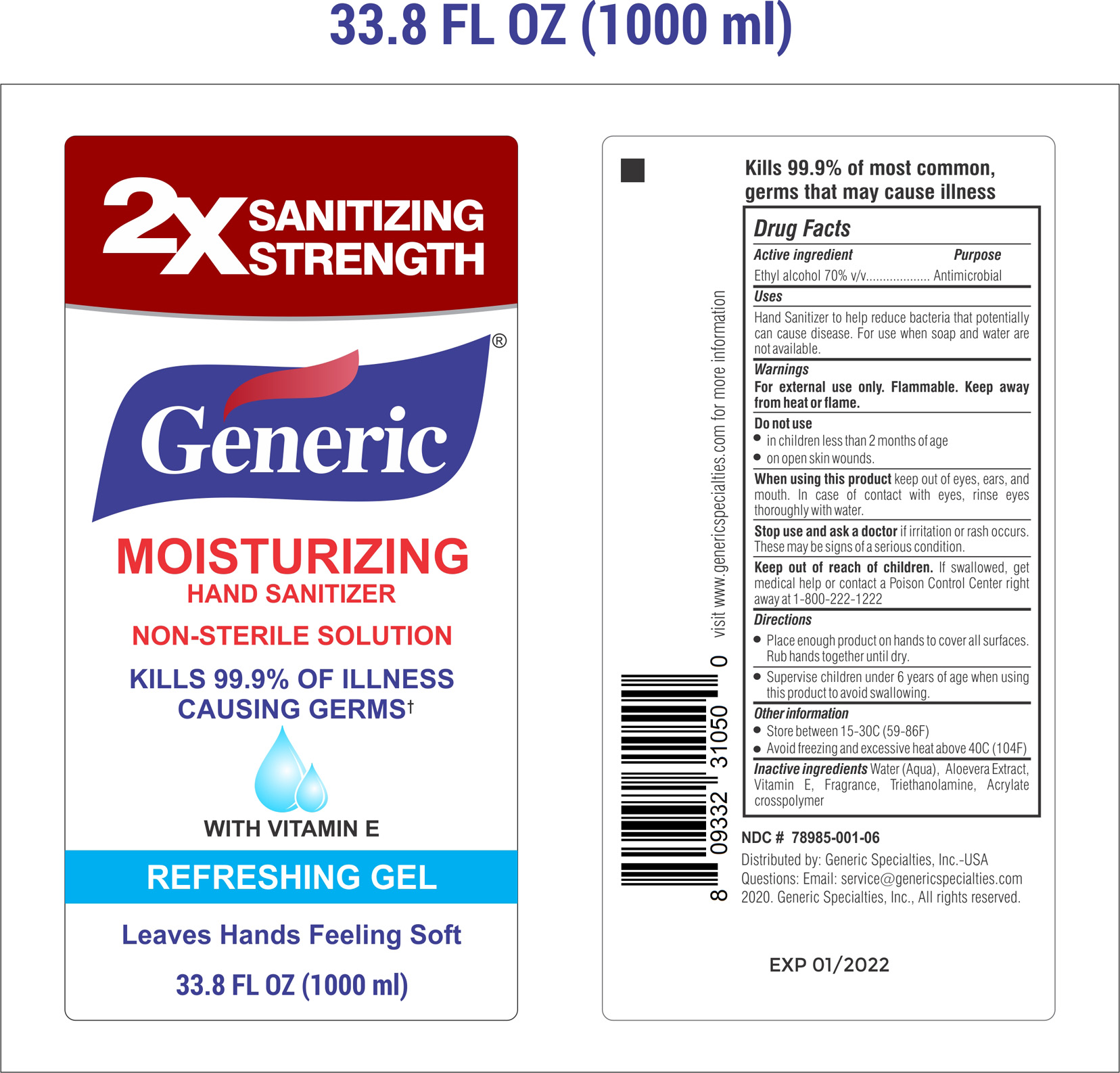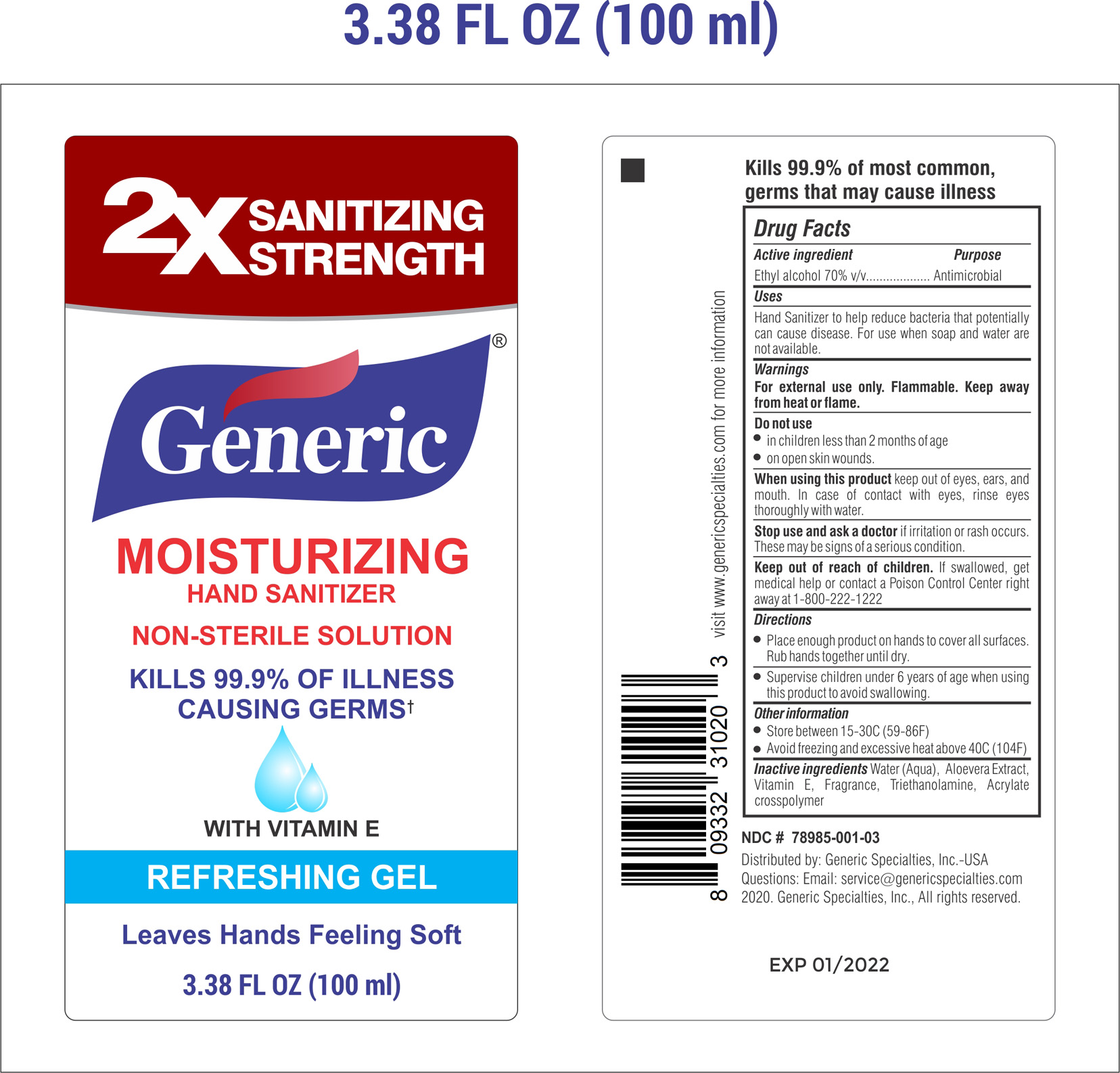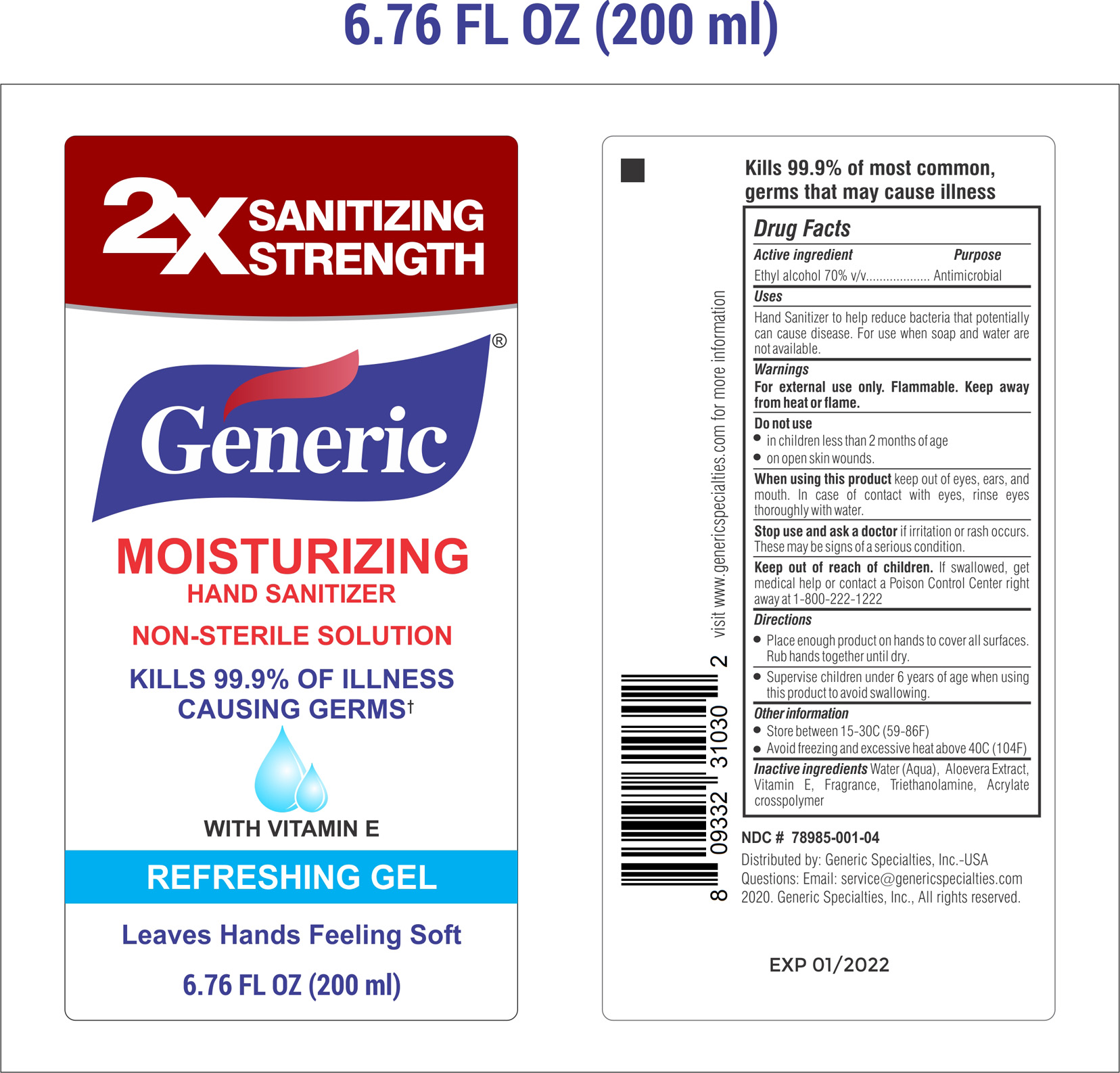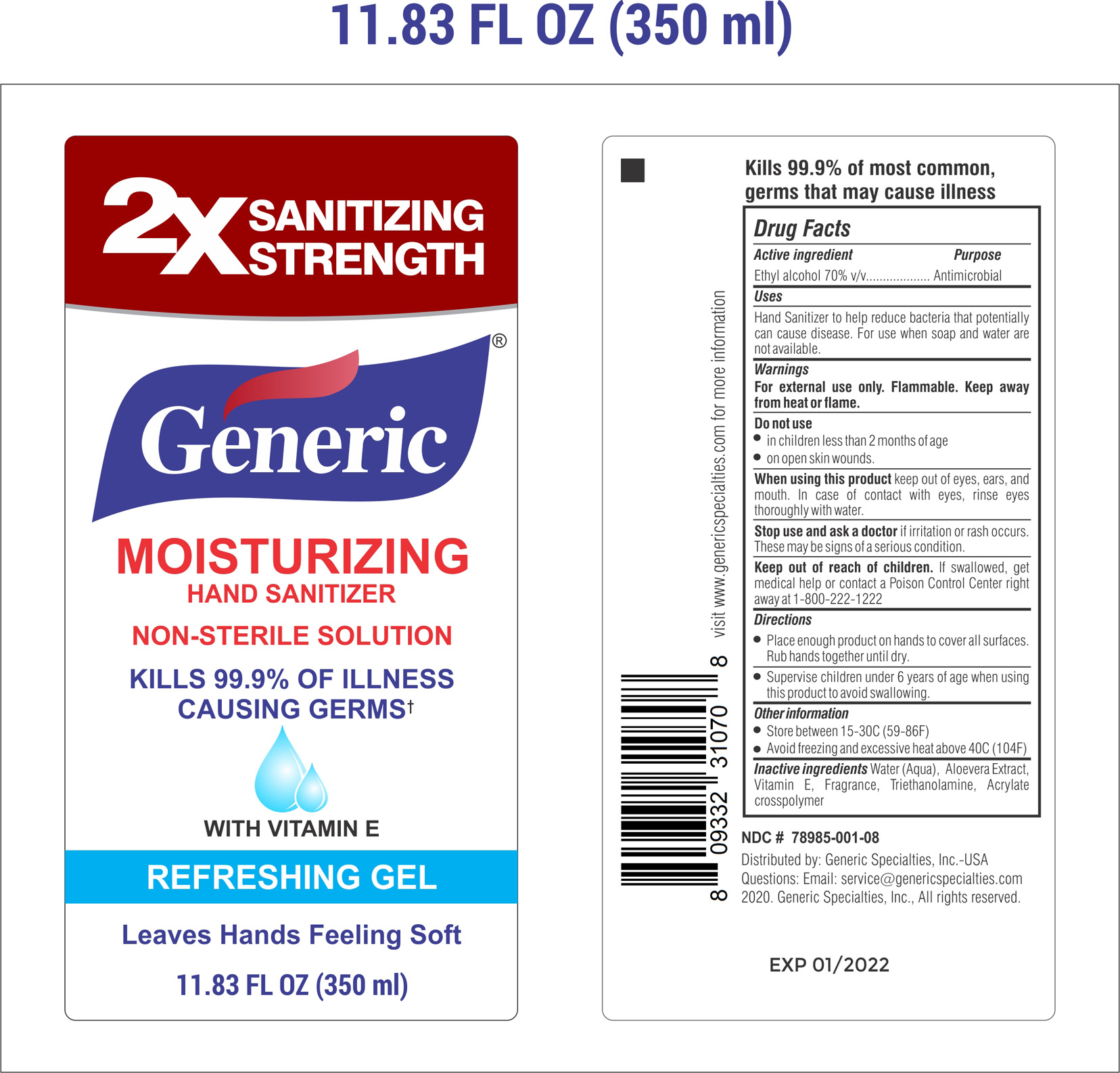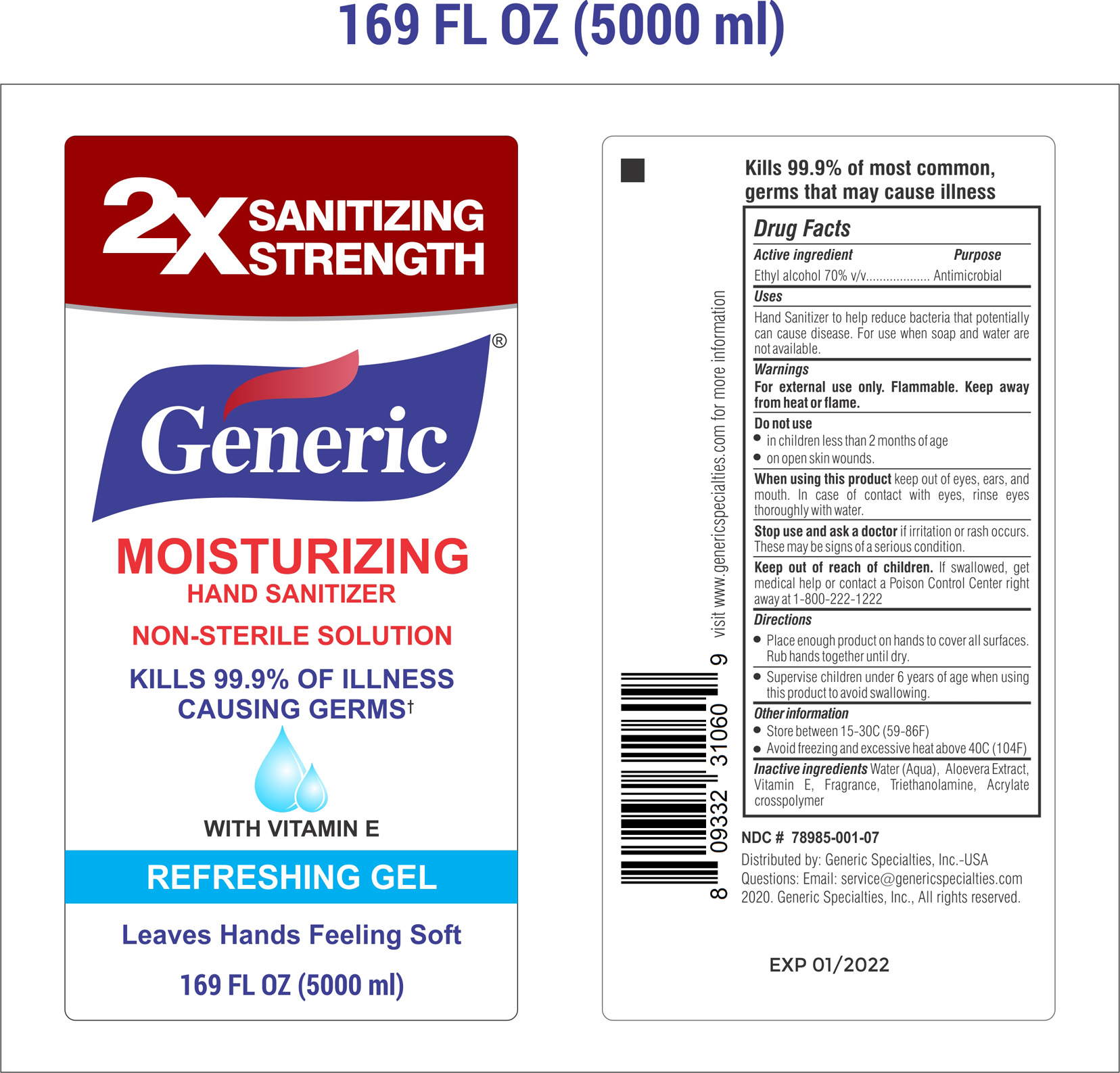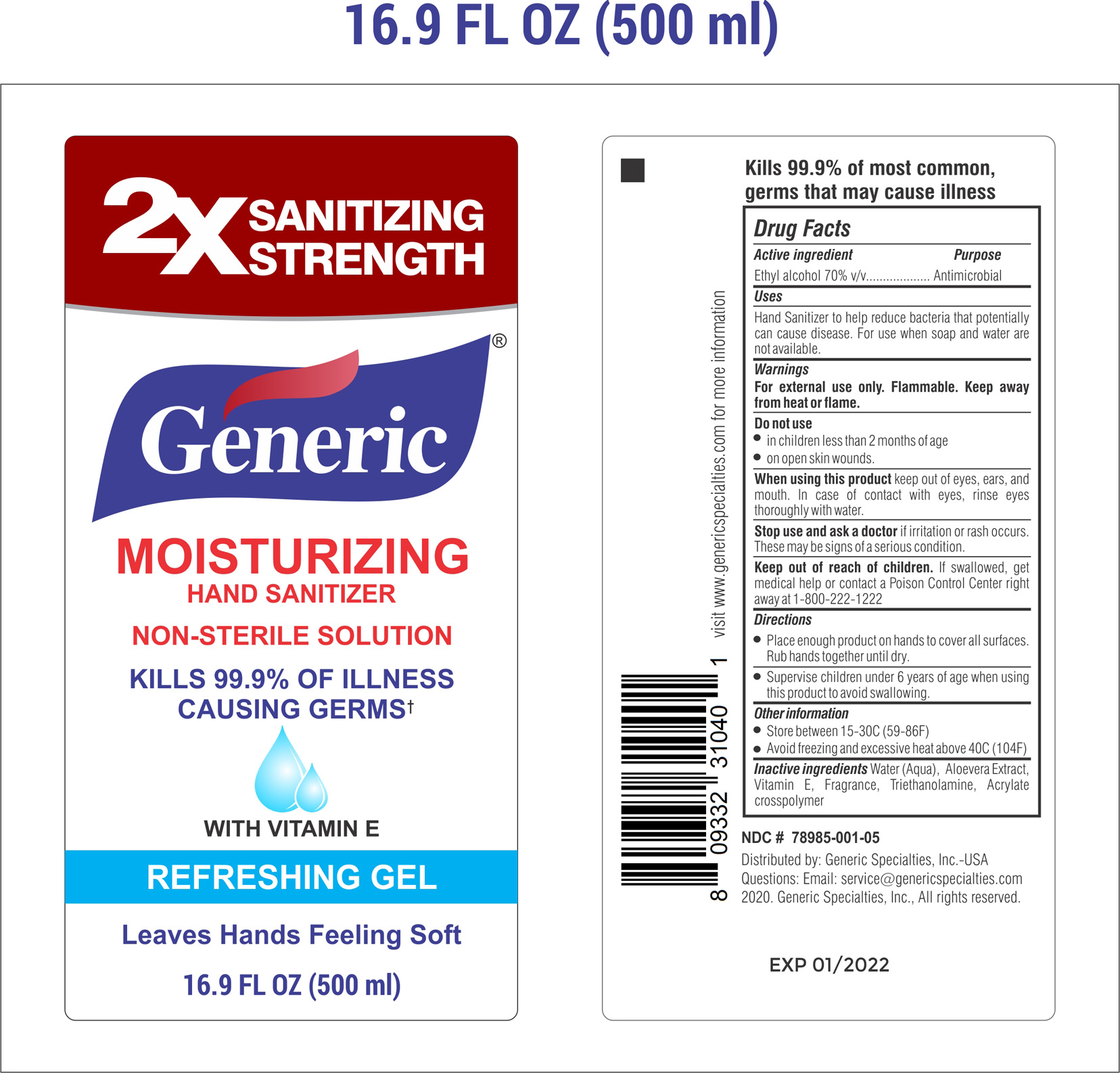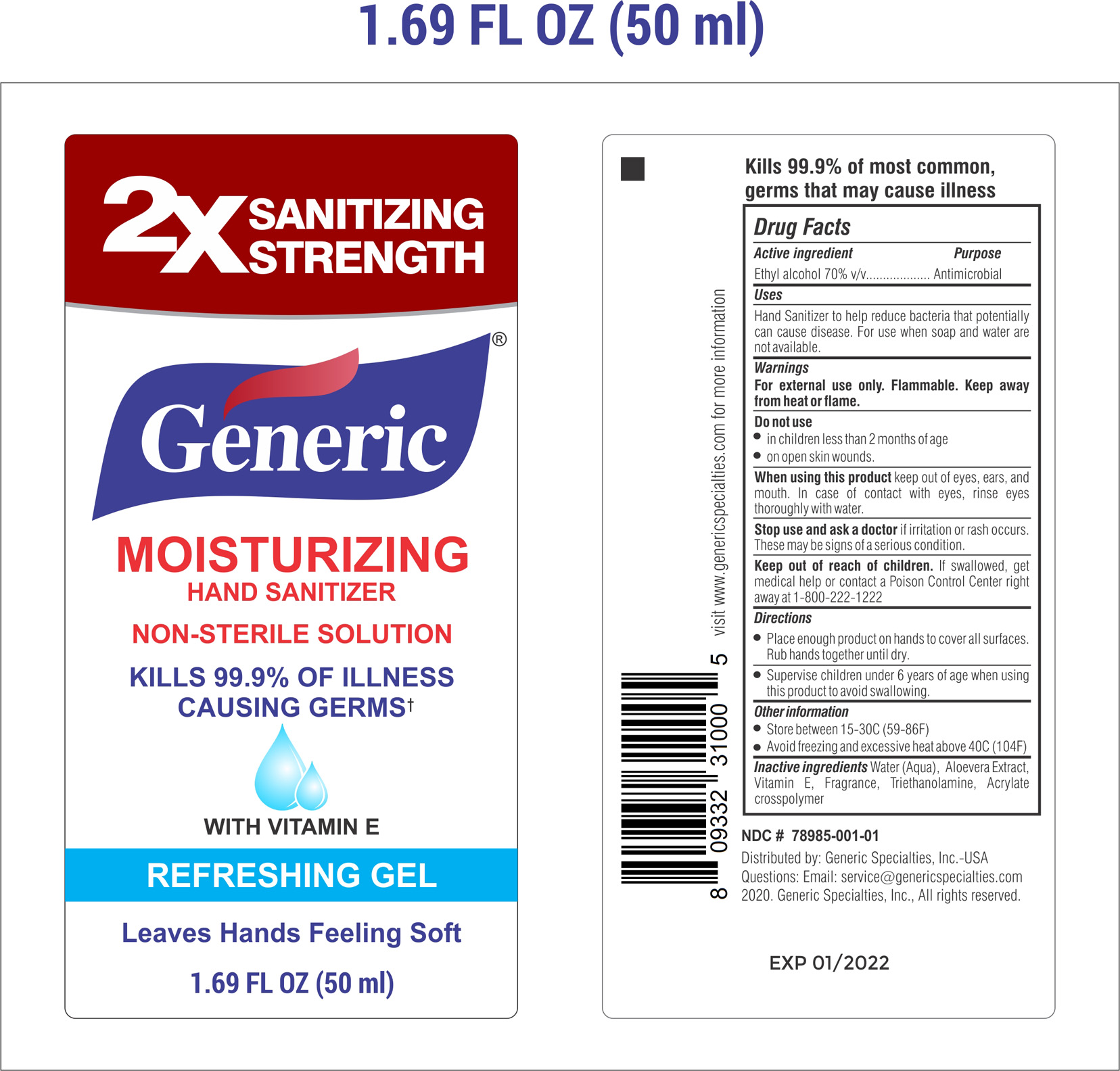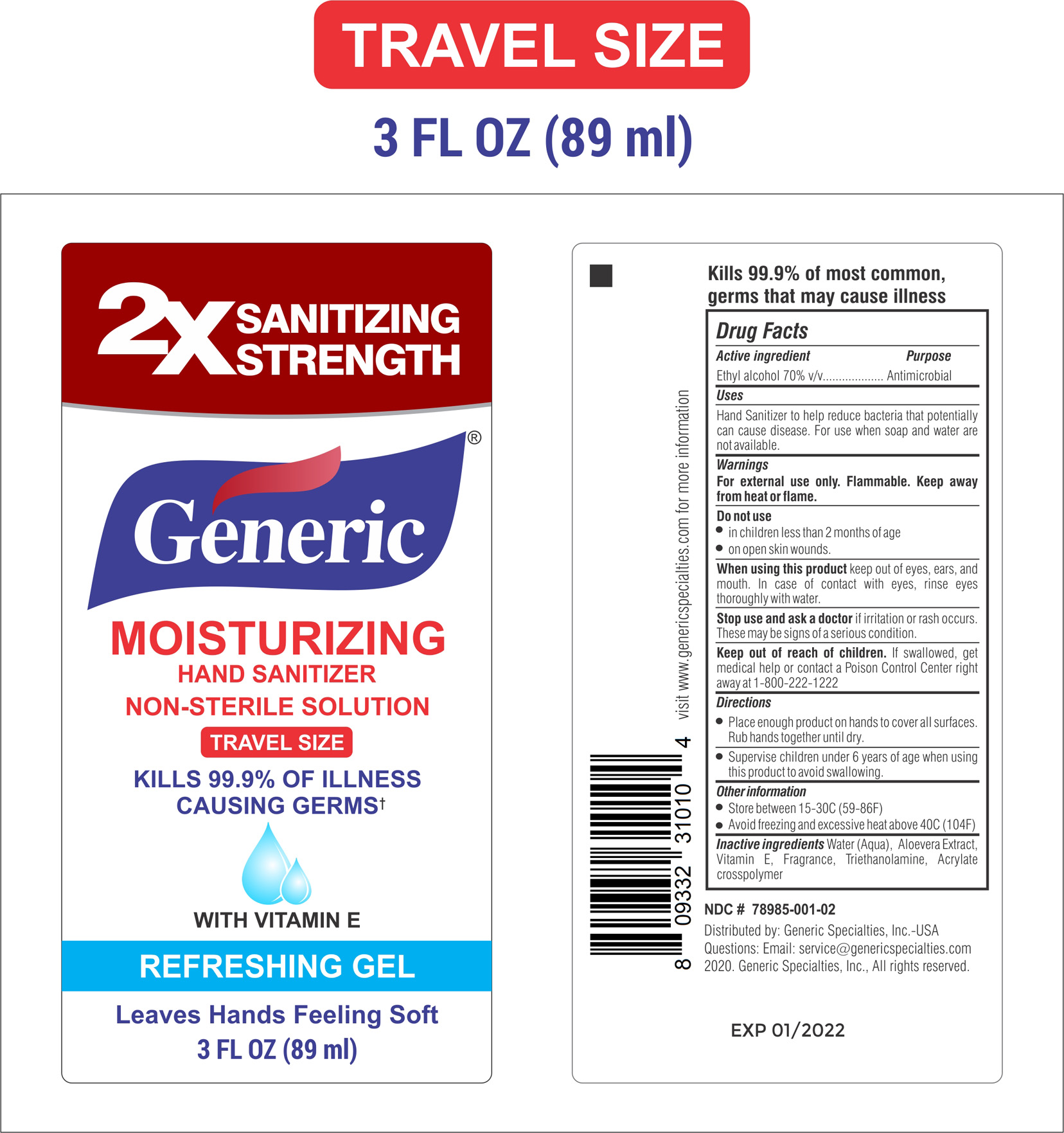 DRUG LABEL: Generic -Hand Sanitizer
NDC: 78985-001 | Form: GEL
Manufacturer: Generic Specialties, Inc.
Category: otc | Type: HUMAN OTC DRUG LABEL
Date: 20200725

ACTIVE INGREDIENTS: ALCOHOL 70 mL/1 1
INACTIVE INGREDIENTS: ALOE VERA LEAF 0.2 mL/1 1; TROLAMINE 0.2 mL/1 1; .ALPHA.-TOCOPHEROL ACETATE 0.2 mL/1 1; CARBOMER HOMOPOLYMER, UNSPECIFIED TYPE 0.6 mL/1 1

This is a hand sanitizer manufactured according to the Temporary Policy for Preparation of Certain Alcohol-Based Hand Sanitizer Products During the Public Health Emergency (CoViD-19); Guidance for Industry.

The hand sanitizer is manufactured using only the following United States Pharmacopoeia (USP) grade ingredients in the preparation of the product (percentage in final product formulation) consistent with World Health Organization (WHO) recommendations:

Alcohol (ethanol) (USP or Food Chemical Codex (FCC) grade) (70%, volume/volume (v/v)) in an aqueous solution denatured according to Alcohol and Tobacco Tax and Trade Bureau regulations in 27 CFR part 20.
Triethanolamine
Vitamin E
Aloevera extract
Acrylate crosspolymer
Fragrance
Sterile distilled water or boiled cold water.

The firm does not add other active or inactive ingredients. Different or additional ingredients may impact the quality and potency of the product.

Active Ingredient(s)

Alcohol 70% v/v. Purpose: Antiseptic

Purpose

Antiseptic, anti-microbial, Hand Sanitizer

See details in the labels attached below....

Use

Hand Sanitizer to help reduce bacteria that potentially can cause disease. For use when soap and water are not available.

Warnings

For external use only. Flammable. Keep away from heat or flame

Do not use

- in children less than 2 months of age
- on open skin wounds

When using this product keep out of eyes, ears, and mouth. In case of contact with eyes, rinse eyes thoroughly with water.

Stop use and ask a doctor if irritation or rash occurs. These may be signs of a serious condition.

Keep out of reach of children. If swallowed, get medical help or contact a Poison Control Center right away at 1-800-222-1222

Directions

- Place enough product on hands to cover all surfaces. Rub hands together until dry.
- Supervise children under 6 years of age when using this product to avoid swallowing.
- As referenced on the product labels.

Other information

- Store between 15-30C (59-86F)
- Avoid freezing and excessive heat above 40C (104F)

Inactive ingredients

Acrylate Crosspolymer, Triethanolamine, Vitamin E, Alovera extract, Ethyl Alcohol, Fragrance, Water

Uses

Hand sanitizer to help reduce bacteria that potentially can cause disease. For use when soap and water are not available.

package label principal display panel

As mentioned below NDC codes

50 ml - 78985-001-01

89 ml - 78985-001-02

100 ml - 78985-001-03

200 ml - 78985-001-04

350 ml - 78985-001-08

500 ml - 78985-001-05

1000 ml - 78985-001-06

5000 ml - 78985-001-07